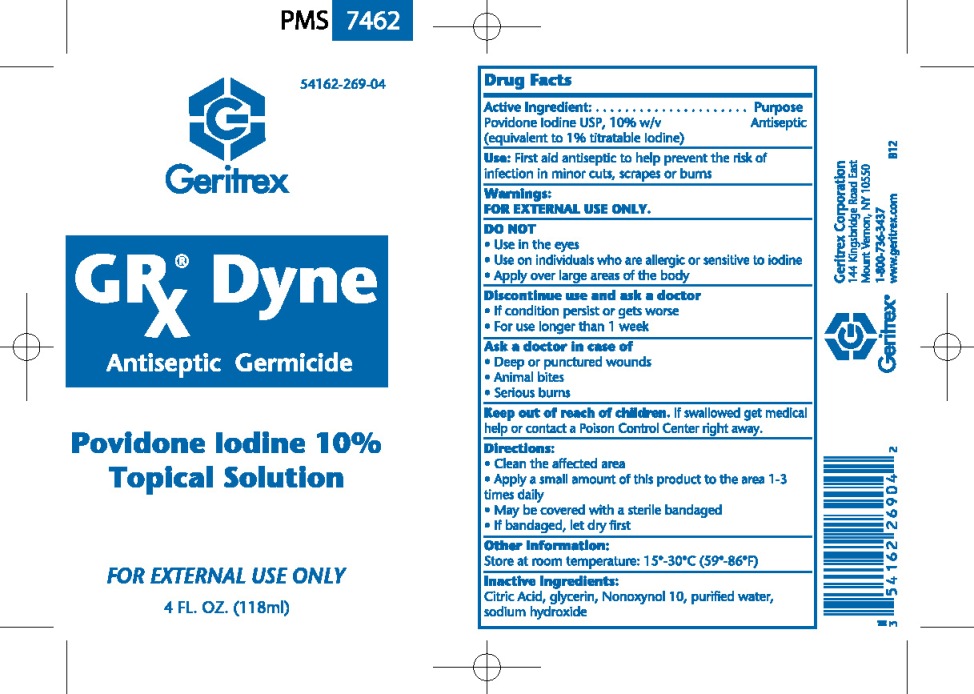 DRUG LABEL: GRx Dyne
NDC: 54162-269 | Form: SOLUTION
Manufacturer: Geritrex Corp.
Category: otc | Type: HUMAN OTC DRUG LABEL
Date: 20120521

ACTIVE INGREDIENTS: POVIDONE-IODINE 10 mL/100 mL
INACTIVE INGREDIENTS: CITRIC ACID MONOHYDRATE; GLYCERIN; NONOXYNOL-10; WATER; SODIUM HYDROXIDE

GRx Dyne Solution

Drug Facts

Active Ingredient: Purpose
Povidone Iodine USP, 10% w/v Antiseptic
(equivalent to 1% titratable Iodine)

Uses

First aid antiseptic to help the risk of infection in
minor cuts, scrapes or burns

Directions

Clean the affected area
Apply a small amount of this product to the area 1-3 times daily
May be covered with a sterile bandaged
If bandaged, let dry first

DOSAGE AND ADMINISTRATION

Apply a small amount of this product to the affected area 1-3 times daily

WARNINGS

FOR EXTERNAL USE ONLY
DO NOT
Use in the eyes
Use on individuals who are allergic of sensitive to iodine
Apply over large areas of the body
Discontinue use and ask a doctor
If condition persist or gets worse
For use longer than 1 week
Ask a doctor in case of
Deep or punctured wounds
Animal bites
Serious burns

INACTIVE INGREDIENT

Citric acid, glycerin, Nonoxynol 10, purified water, sodium hydroxide

STORAGE AND HANDLING

Store at room temperature: 15'-30'C (59'-86'F)

keep out of reach of children. If swallowed get medical help
or contact a Poison Control Center right away.

PACKAGE LABEL

Enter section text here